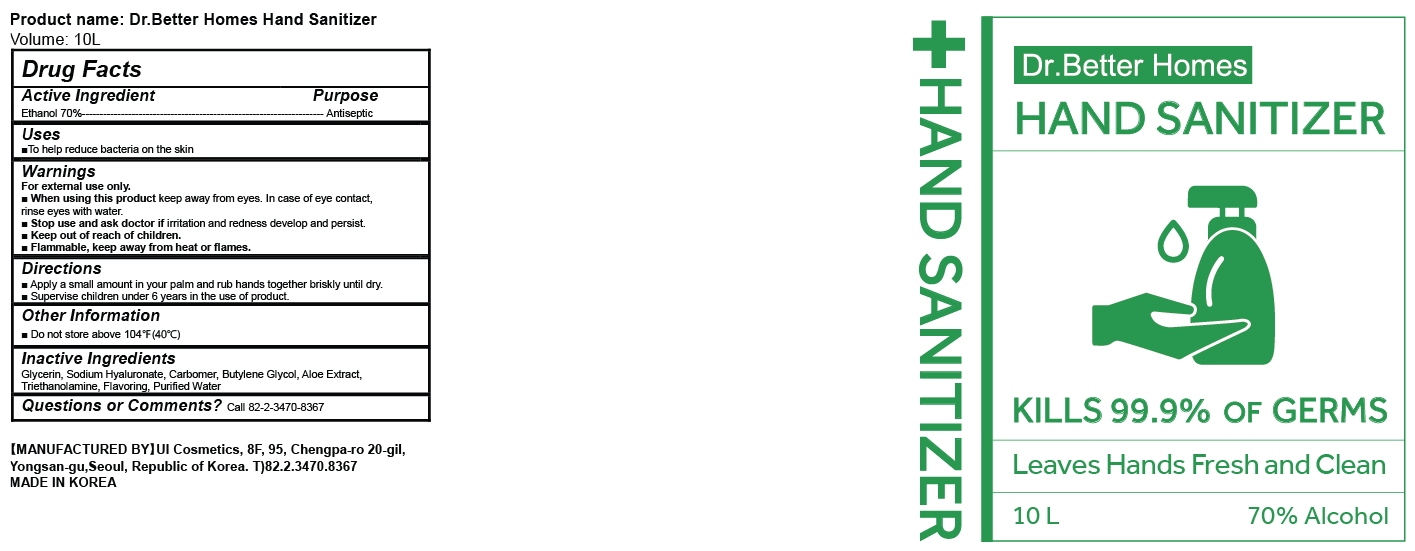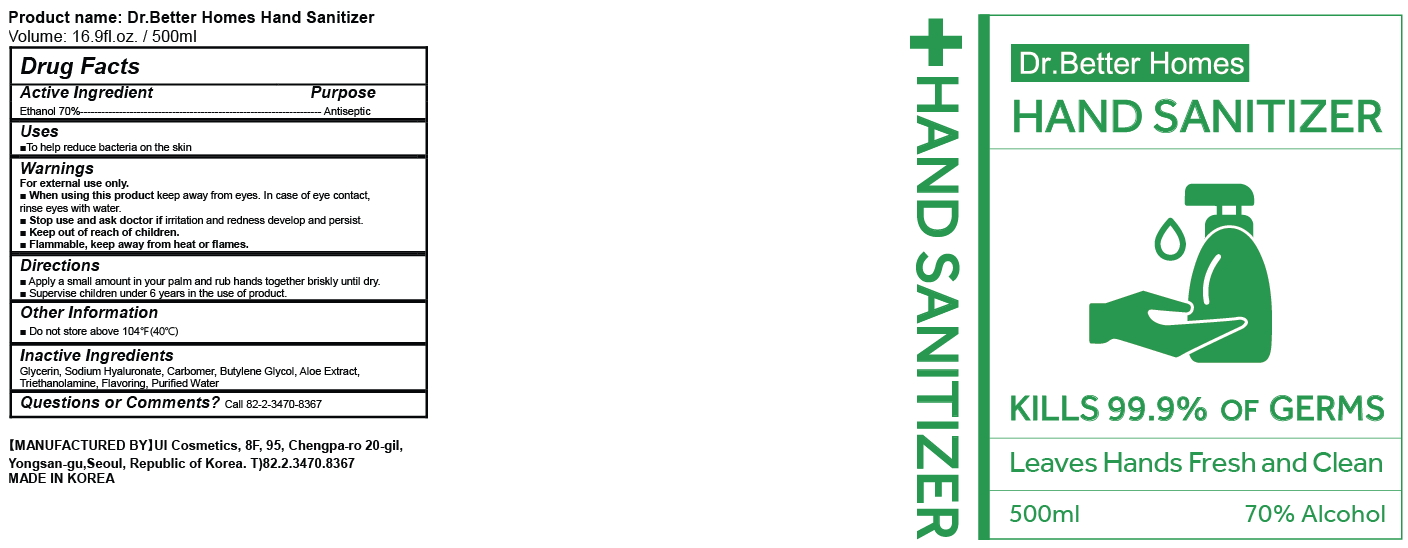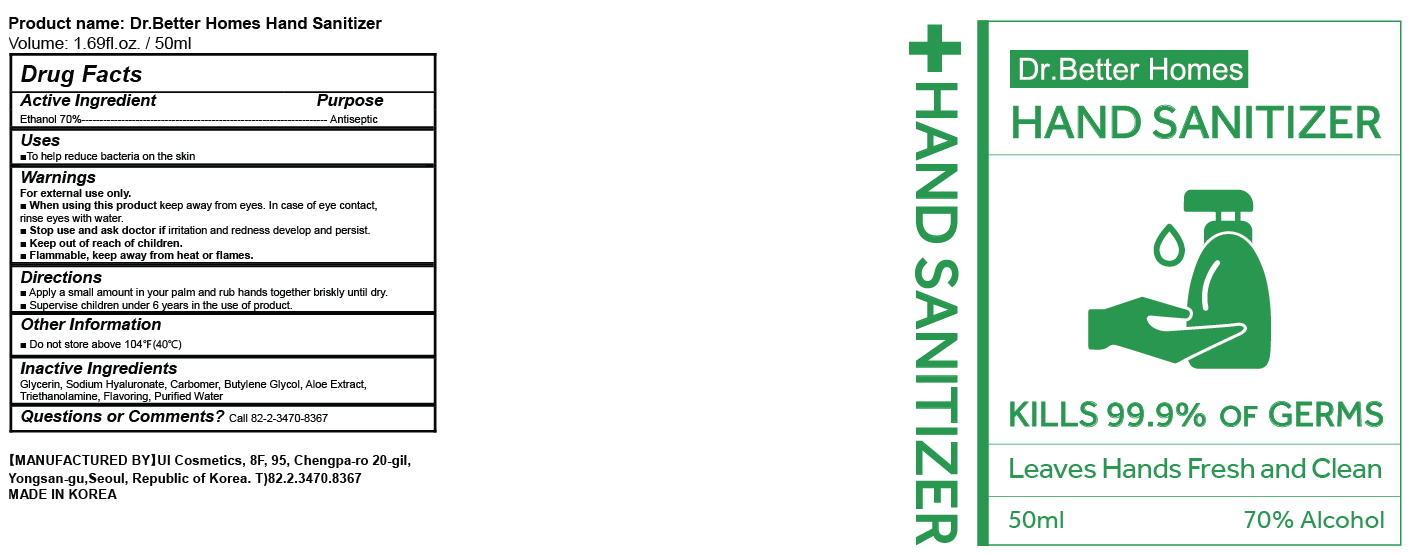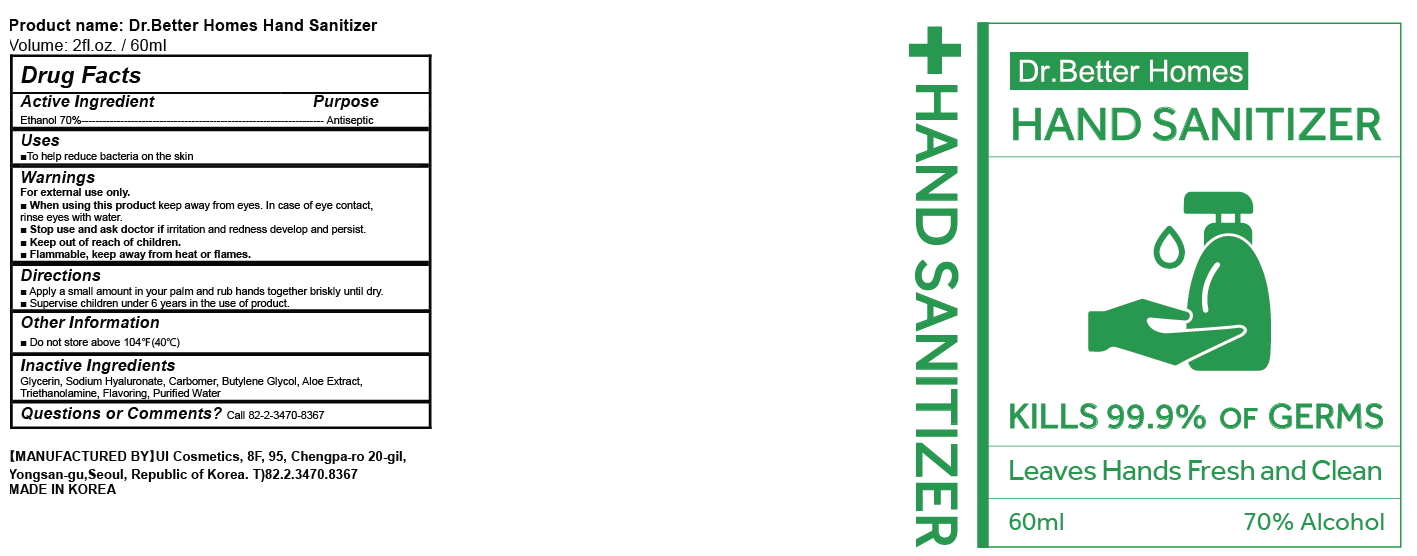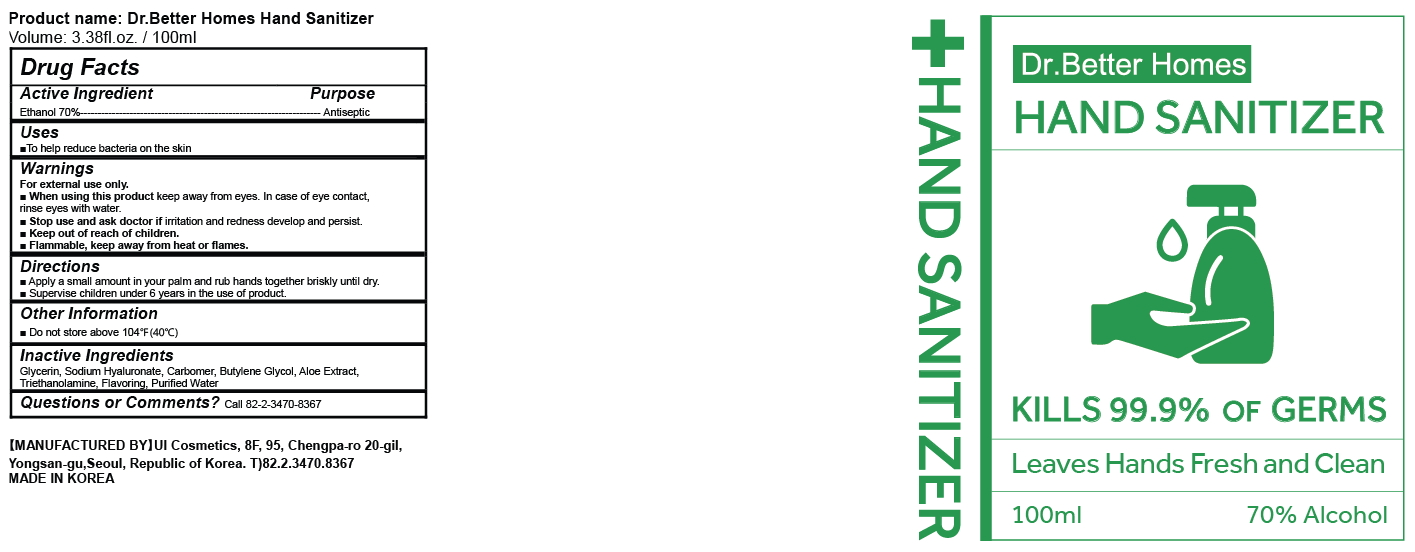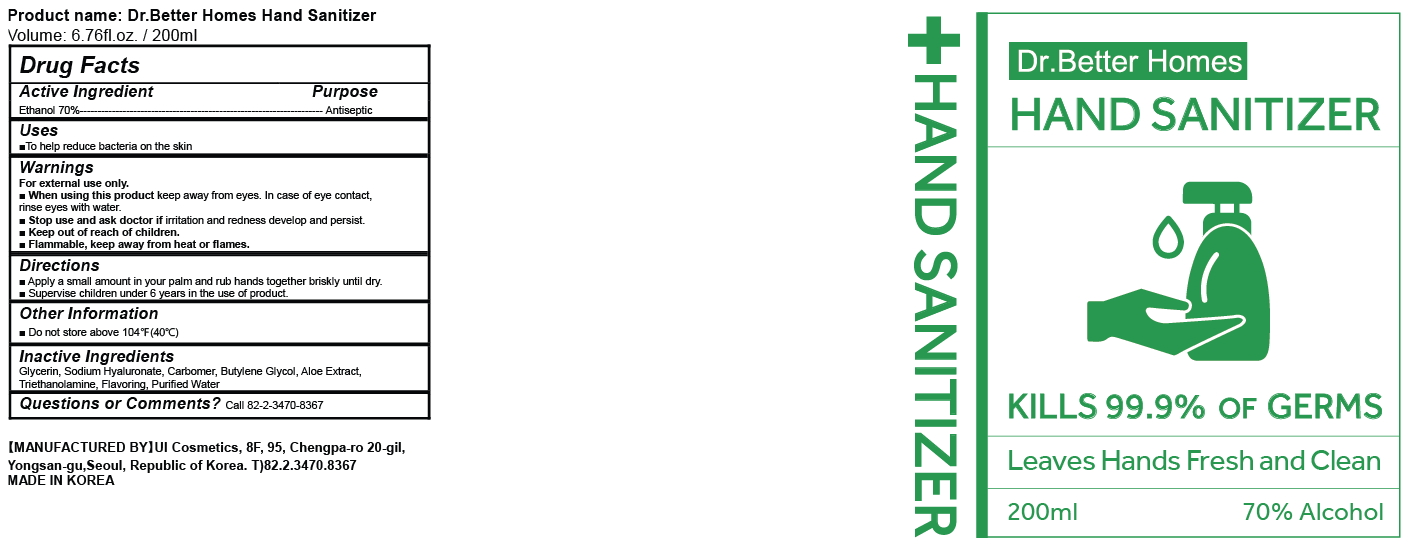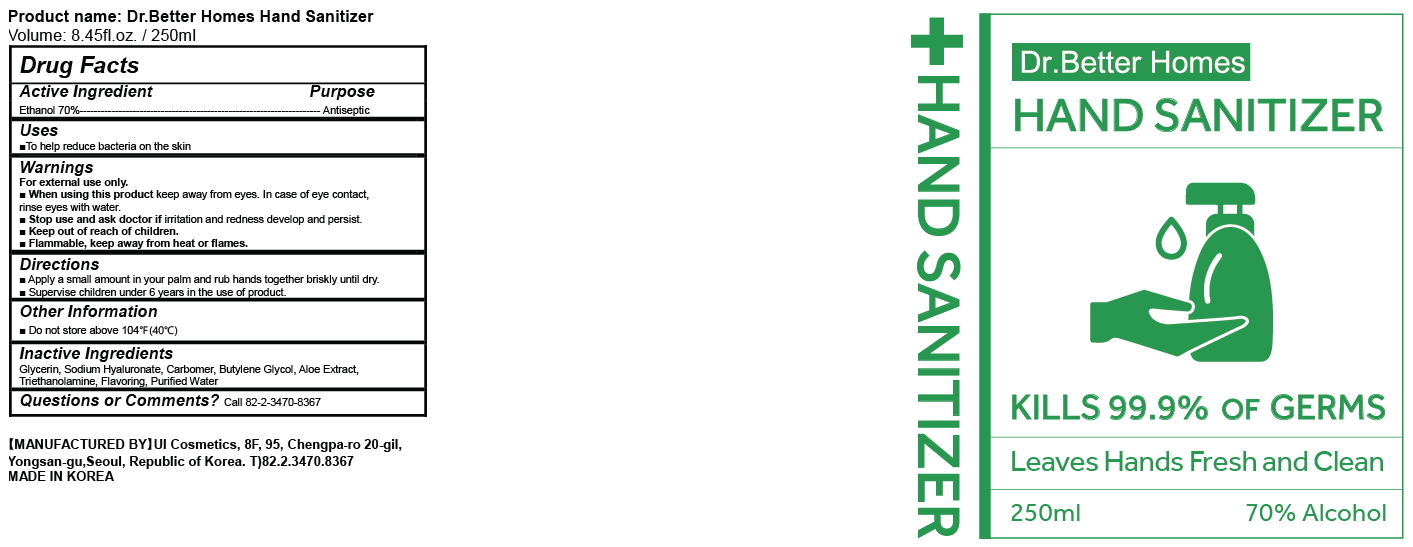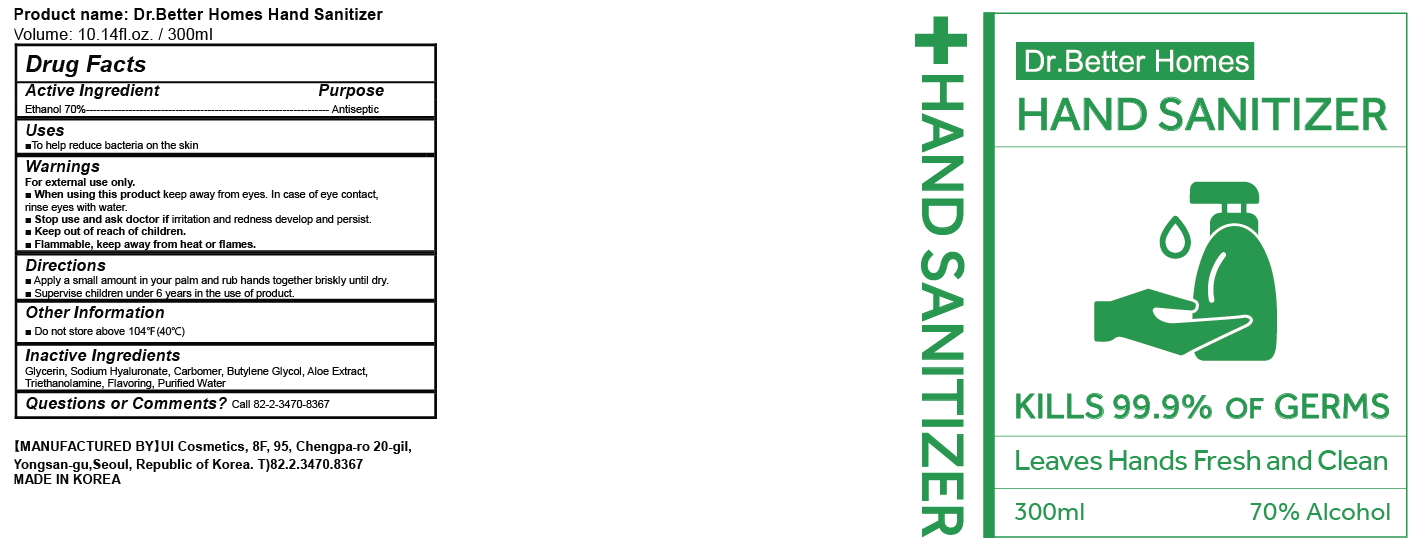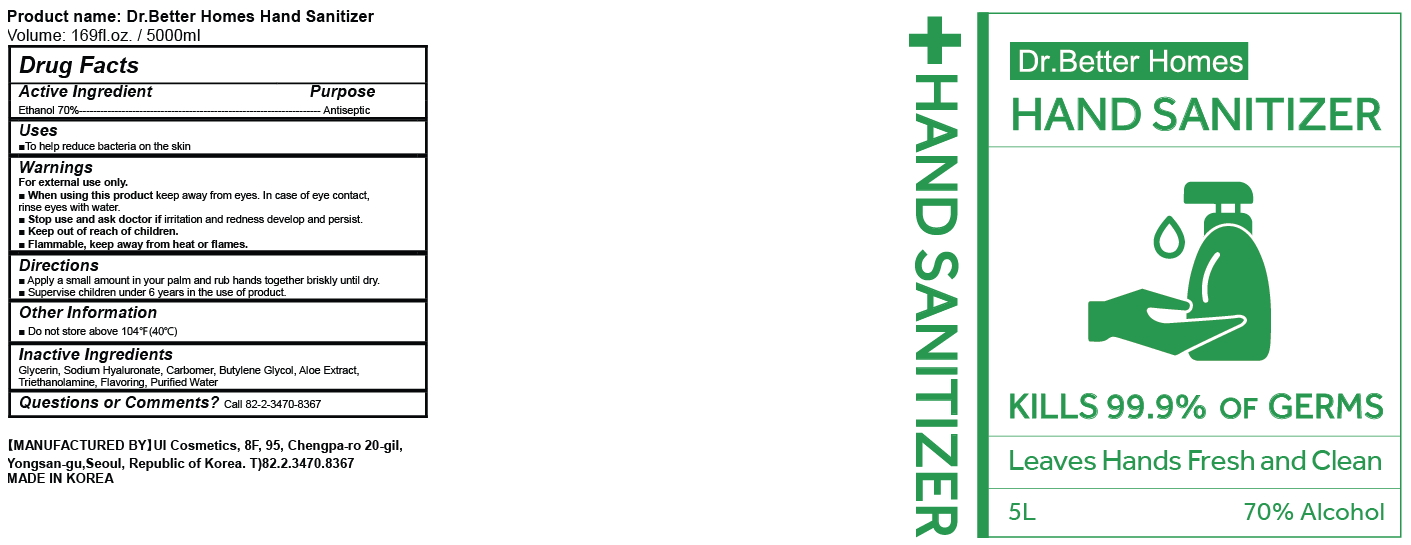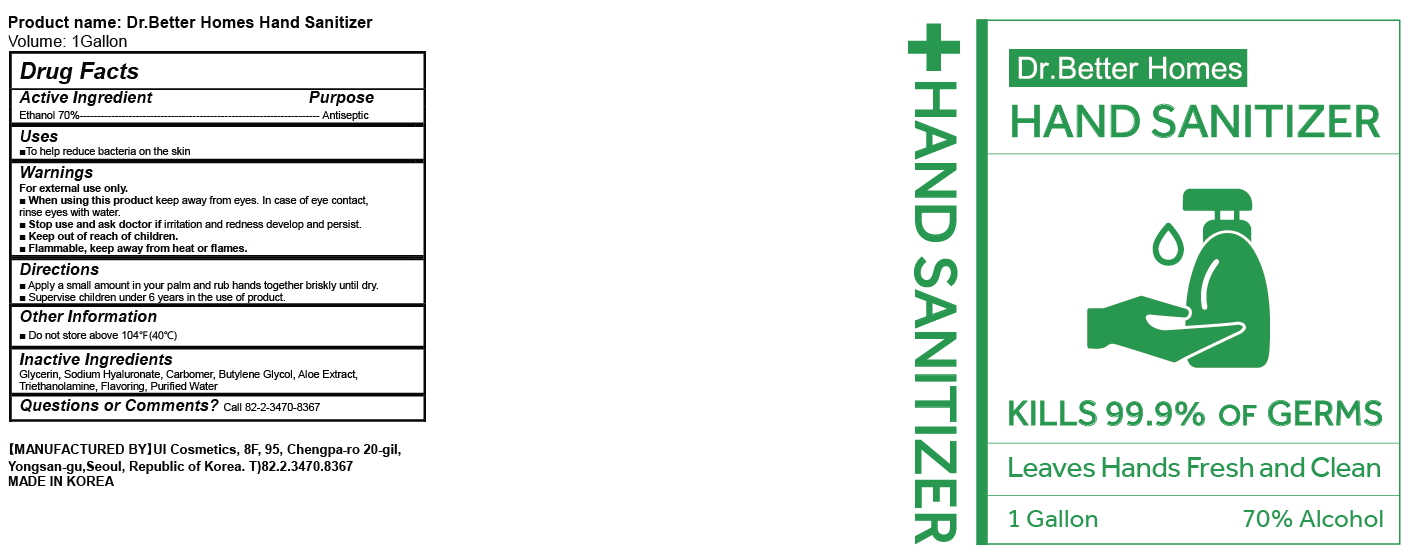 DRUG LABEL: Dr.Better Homes HAND SANITIZER
NDC: 75615-0020 | Form: GEL
Manufacturer: UI COSMETICS CO., LTD
Category: otc | Type: HUMAN OTC DRUG LABEL
Date: 20210121

ACTIVE INGREDIENTS: ALCOHOL 70 mL/100 mL
INACTIVE INGREDIENTS: GLYCERIN; HYALURONATE SODIUM; FRAGRANCE LAVENDER & CHIA F-153480; WATER; CARBOMER HOMOPOLYMER, UNSPECIFIED TYPE; BUTYLENE GLYCOL; ALOE; TROLAMINE

Active Ingredient

Ethanol 70%

Purpose

Antiseptic

Uses

To help reduce bacteria on the skin

Warnings

For external use only.

Flammable, keep away from heat or flames.

When using this product

keep away from eyes. In case of eye contact, rinse eyes with water.

Stop use and ask doctor if

irritation and redness develop and persist.

Directions

Apply a small amount in your palm and rub hands together briskly until dry.

Supervise children under 6 years in the use of product.

Other Information

Protect this product from excessive heat and direct sun.

Inactive Ingredients

Glycerin, Sodium Hyaluronate, Carbomer, Butylene Glycol, Aloe Extract, Triethanolamine, Flavoring, Purified Water